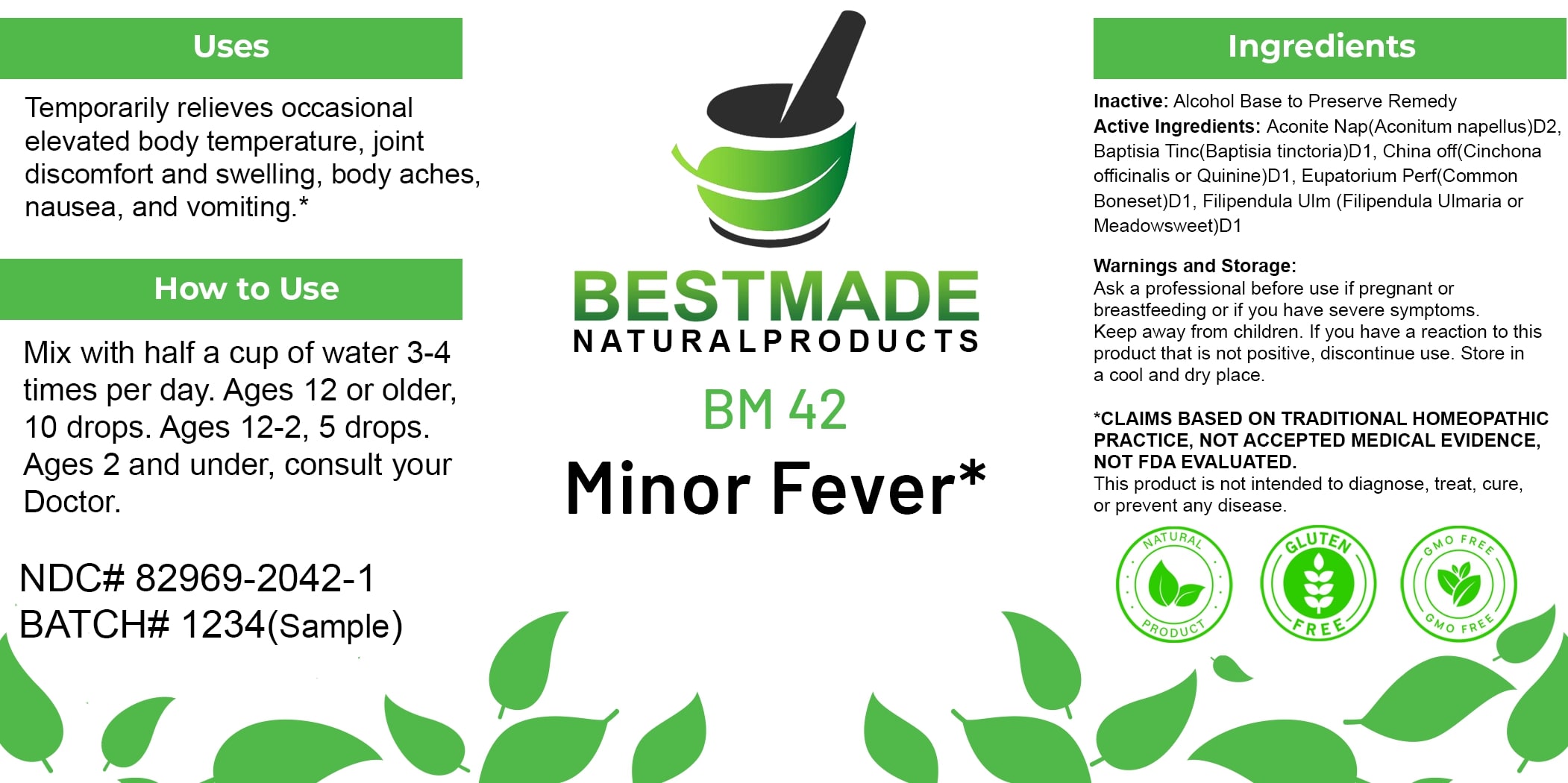 DRUG LABEL: Bestmade Natural Products BM42
NDC: 82969-2042 | Form: LIQUID
Manufacturer: Bestmade Natural Products
Category: homeopathic | Type: HUMAN OTC DRUG LABEL
Date: 20250123

ACTIVE INGREDIENTS: BAPTISIA TINCTORIA 30 [hp_C]/30 [hp_C]; EUPATORIUM PERFOLIATUM FLOWERING TOP 30 [hp_C]/30 [hp_C]; ACONITUM NAPELLUS 30 [hp_C]/30 [hp_C]; CINCHONA OFFICINALIS BARK 30 [hp_C]/30 [hp_C]; FILIPENDULA ULMARIA ROOT 30 [hp_C]/30 [hp_C]
INACTIVE INGREDIENTS: ALCOHOL 30 [hp_C]/30 [hp_C]

BM42

DOSAGE AND ADMINISTRATION

How to Use

Mix with half a cup of water 3-4 times per day. Ages 12 or older, 10 drops. Ages 12-2, 5 drops. Ages 2 and under, consult your Doctor.

INACTIVE INGREDIENT

Ingredients

Inactive: Alcohol Base to Preserve Remedy

Uses

Temporarily relieves occasional elevated body temperature, joint discomfort and swelling, body aches, nausea, and vomiting.*

*CLAIMS BASED ON TRADITIONAL HOMEOPATHIC PRACTICE, NOT ACCEPTED MEDICAL EVIDENCE, NOT FDA EVALUATED.

This product is not intended to diagnose, treat, cure, or prevent any disease.

Uses

Temporarily relieves occasional elevated body temperature, joint discomfort and swelling, body aches, nausea, and vomiting.*

*CLAIMS BASED ON TRADITIONAL HOMEOPATHIC PRACTICE, NOT ACCEPTED MEDICAL EVIDENCE, NOT FDA EVALUATED.

This product is not intended to diagnose, treat, cure, or prevent any disease.

KEEP OUT OF REACH OF CHILDREN

Warnings and Storage:

Ask a professional before use if pregnant or breastfeeding or if you have severe symptoms. Keep away from children. If you have a reaction to this product that is not positive, discontinue use. Store in a cool and dry place.

ACTIVE INGREDIENT

Active Ingredients: Aconite Nap (Aconitum napellus) D2, Baptisia Tinc (Baptisia tinctoria) D1, China off (Cinchona officinalis or Quinine) D1, Eupatorium Perf (Common Boneset) D1, Filipendula Ulm (Filipendula Ulmaria or Meadowsweet) D1

Warnings and Storage:

Ask a professional before use if pregnant or breastfeeding or if you have severe symptoms. Keep away from children. If you have a reaction to this product that is not positive, discontinue use. Store in a cool and dry place.

*CLAIMS BASED ON TRADITIONAL HOMEOPATHIC PRACTICE, NOT ACCEPTED MEDICAL EVIDENCE, NOT FDA EVALUATED.

This product is not intended to diagnose, treat, cure, or prevent any disease.

Entire package label